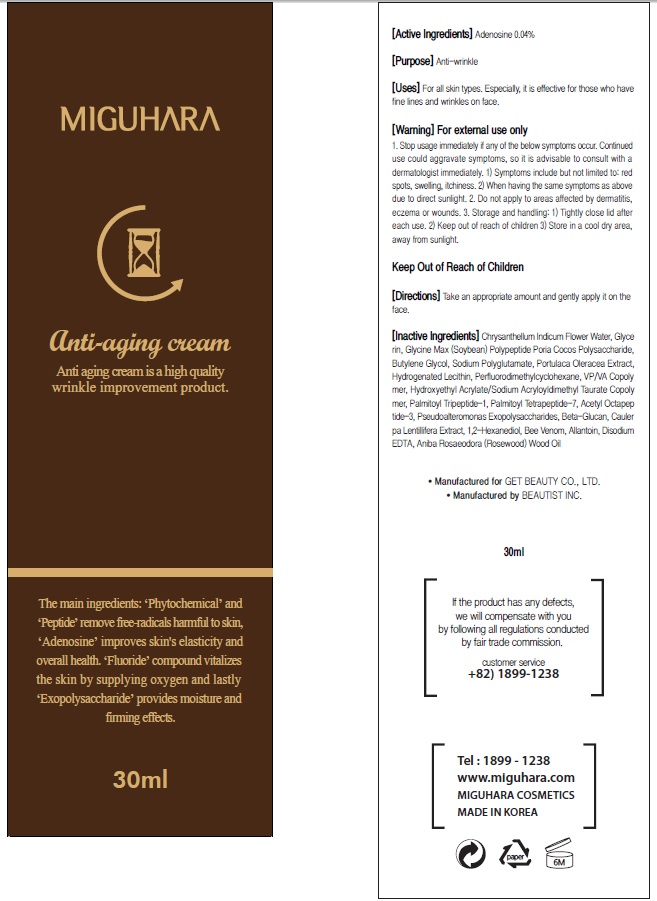 DRUG LABEL: Anti aging
NDC: 71477-020 | Form: CREAM
Manufacturer: Get Beauty
Category: otc | Type: HUMAN OTC DRUG LABEL
Date: 20170619

ACTIVE INGREDIENTS: Adenosine 0.012 g/30 mL
INACTIVE INGREDIENTS: Glycerin; Butylene Glycol

ACTIVE INGREDIENT

Active ingredients: Adenosine 0.04%

INACTIVE INGREDIENT

Inactive Ingredients: Chrysanthellum Indicum Flower Water, Glycerin, Glycine Max (Soybean) Polypeptide, Poria Cocos Polysaccharide, Butylene Glycol, Sodium Polyglutamate, Portulaca Oleracea Extract, Hydrogenated Lecithin, Perfluorodimethylcyclohexane, VP/VA Copolymer, Hydroxyethyl Acrylate/Sodium Acryloyldimethyl Taurate Copolymer, Palmitoyl Tripeptide-1, Palmitoyl Tetrapeptide-7, Acetyl Octapeptide-3, Pseudoalteromonas Exopolysaccharides, Beta-Glucan, Caulerpa Lentillifera Extract, 1,2-Hexanediol, Bee Venom, Allantoin, Disodium EDTA, Aniba Rosaeodora (Rosewood) Wood Oil

PURPOSE

Purpose: Anti-wrinkle

WARNINGS

Warning: For external use only 1. Stop usage immediately if any of the below symptoms occur. Continued use could aggravate symptoms, so it is advisable to consult with a dermatologist immediately. 1) Symptoms include but not limited to: red spots, swelling, itchiness. 2) When having the same symptoms as above due to direct sunlight. 2. Do not apply to areas affected by dermatitis, eczema or wounds. 3. Storage and handling: 1) Tightly close lid after each use. 2 Keep out of reach of children 3) Store in a cool dry area, away from sunlight

KEEP OUT OF REACH OF CHILDREN

Uses

Uses: For all skin types. Especially, it is effective for those who have fine lines and wrinkles on face.

Directions

Directions: Take an appropriate amount and gently apply it on the face.